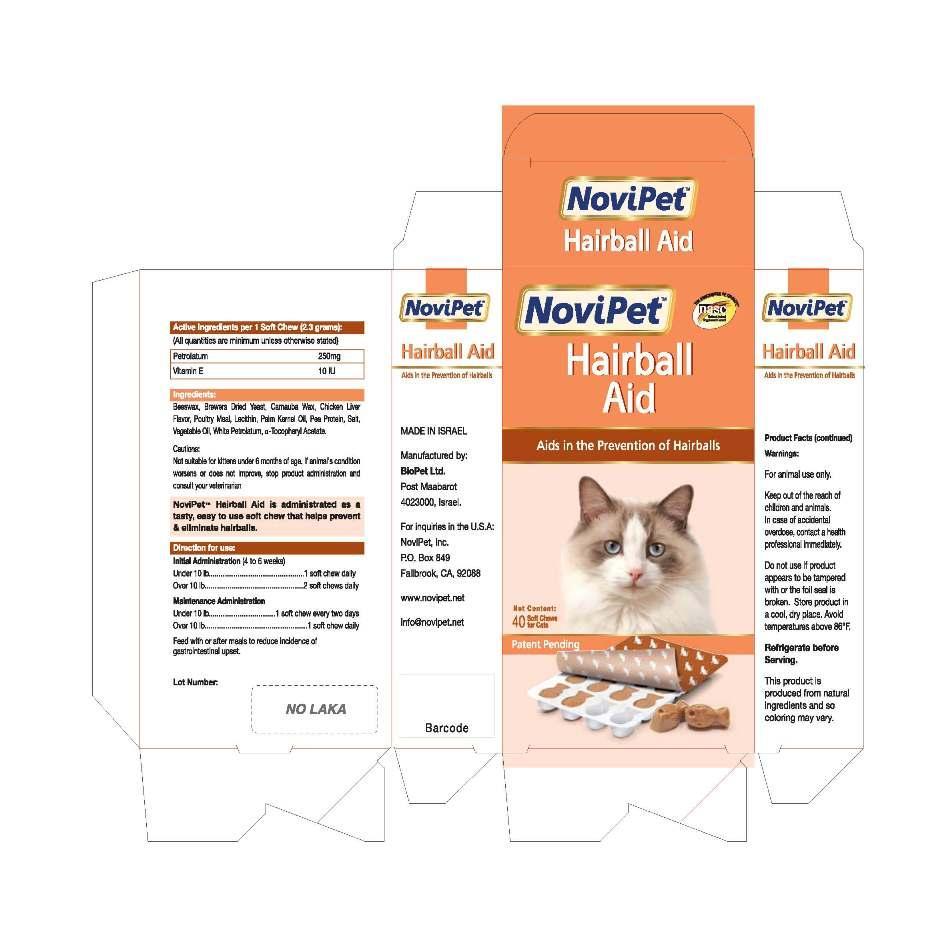 DRUG LABEL: Hairball Aid
                
NDC: 45732-026 | Form: TABLET, CHEWABLE
Manufacturer: Novipet, Inc.
Category: animal | Type: OTC ANIMAL DRUG LABEL
Date: 20121029

ACTIVE INGREDIENTS: PETROLATUM 250 mg/1 1; TOCOPHEROL 10 [iU]/1 1

NoviPet Hairball Aid

CARTON FRONT PANEL

NoviPet

Hairball

Aid

Aids in the Prevention of Hairballs

Net Contents: 40 Soft Chews for Cats

Patent Pending

CARTON LEFT SIDE PANEL

NoviPet Hairball Aid

Aids in the Prevention of Hairballs

MADE IN ISRAEL
Manufactured by:
BioPet Ltd.
Post Maabarot
4023000, Israel
For inquiries in the U.S.A:
NOVIPET,Inc.
P.O. BOX 849
FALLBROOK, CA 92088
www.novipet.net
info@novipet.net

CARTON RIGHT SIDE PANEL

NoviPet

Hairball Aid

Aids in the Prevention of Hairballs

Product Facts (continued)
Warnings
For animal use only.
Keep out of the reach of
children and animals.
In case of accidental
overdose, contact a health
professional immediately.
Do not use if product
appears to be tampered
with or the foil seal is
broken. Store product in
a cool, dry place. Avoid
temperatures above 86^0F.
Refrigerate before
Serving.
This product is
produced from natural
ingredients and so
coloring may vary.

ACTIVE INGREDIENT

Active Ingredients per 1 Soft Chew (2.3 grams):

(All quantities are minimum unless otherwise stated)
Petrolatum 250mg
Vitamin E 10 lU

INACTIVE INGREDIENT

Ingredients:
Beeswax, Brewers Dried Yeast, Carnuba Wax, Chicken Liver
Flavor, Poultry Meat, Lecithin, Palm Kernel Oil, Pea Protein, Salt,
Vegetable Oil, White PetroIatum, a-Tocopheryl Acetate.

PRECAUTIONS

Cautions:
Not suitable for kittens under 6 months of age. If animal's condition
worsens or does not improve, stop product administration and
consult your veterinarian

NoviPet- Hairball Aid is administrated as
a tasty, easy to use soft chew that helps
prevent and eliminate halrballs

Directions for use:

Initial Administration (4 to 6 weeks)
Under 10 Ib .................................................. l soft chew daily

Over 10 Ib ................................................... 2 soft chews daily

Maintenance Administration
Under 10 Ib ................................... l soft chew every two days

Over 10 Ib ...................................................... l soft chew daily

Feed with or after meals to reduce incidence of
gastrointestinal upset.
Lot Number:

Do not use if product
appears to be tampered
with or the foil seal is
broken. Store product in
a cool, dry place. Avoid
temperatures above 86^0F.

Refrigerate before
Serving.

Carton label